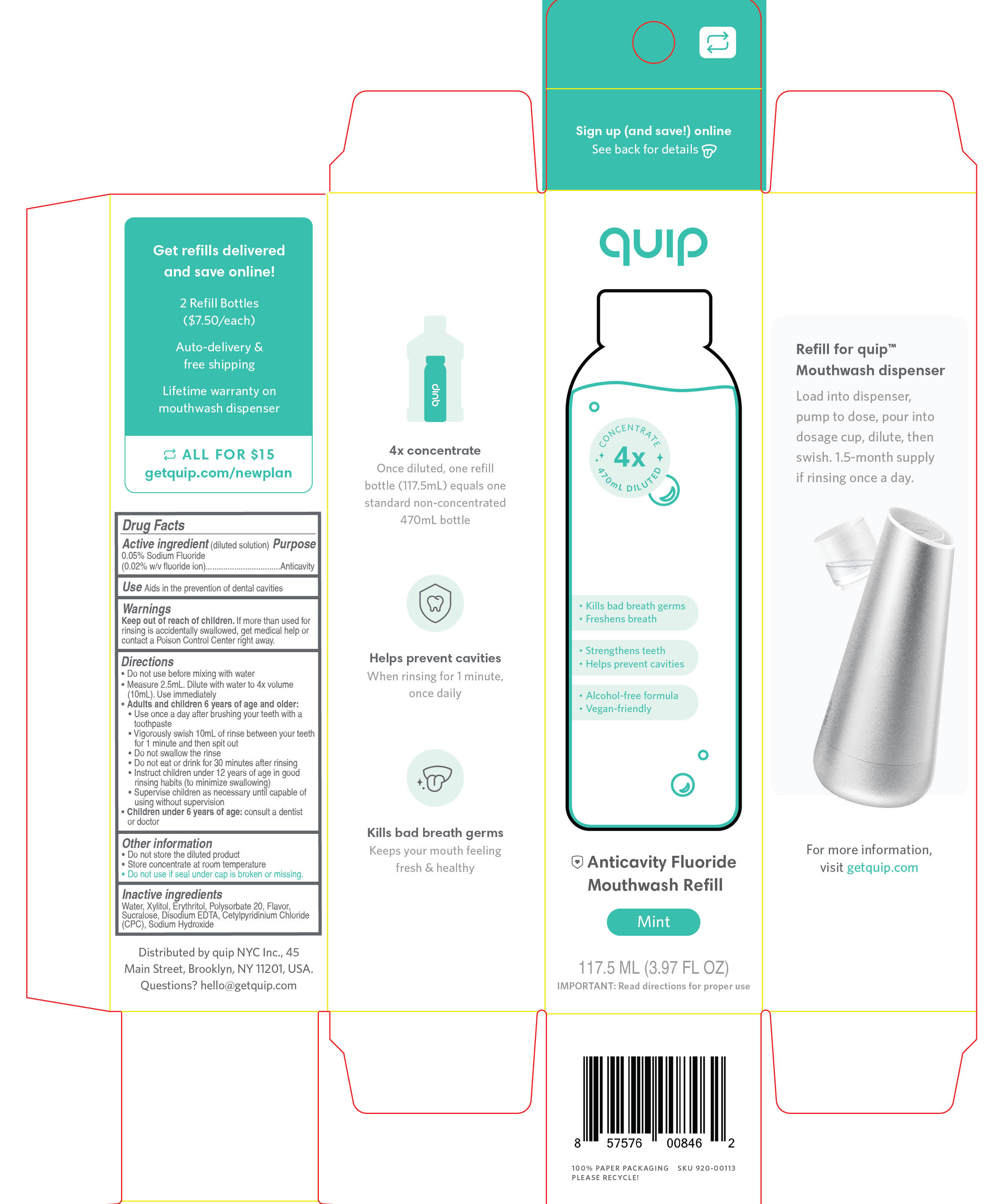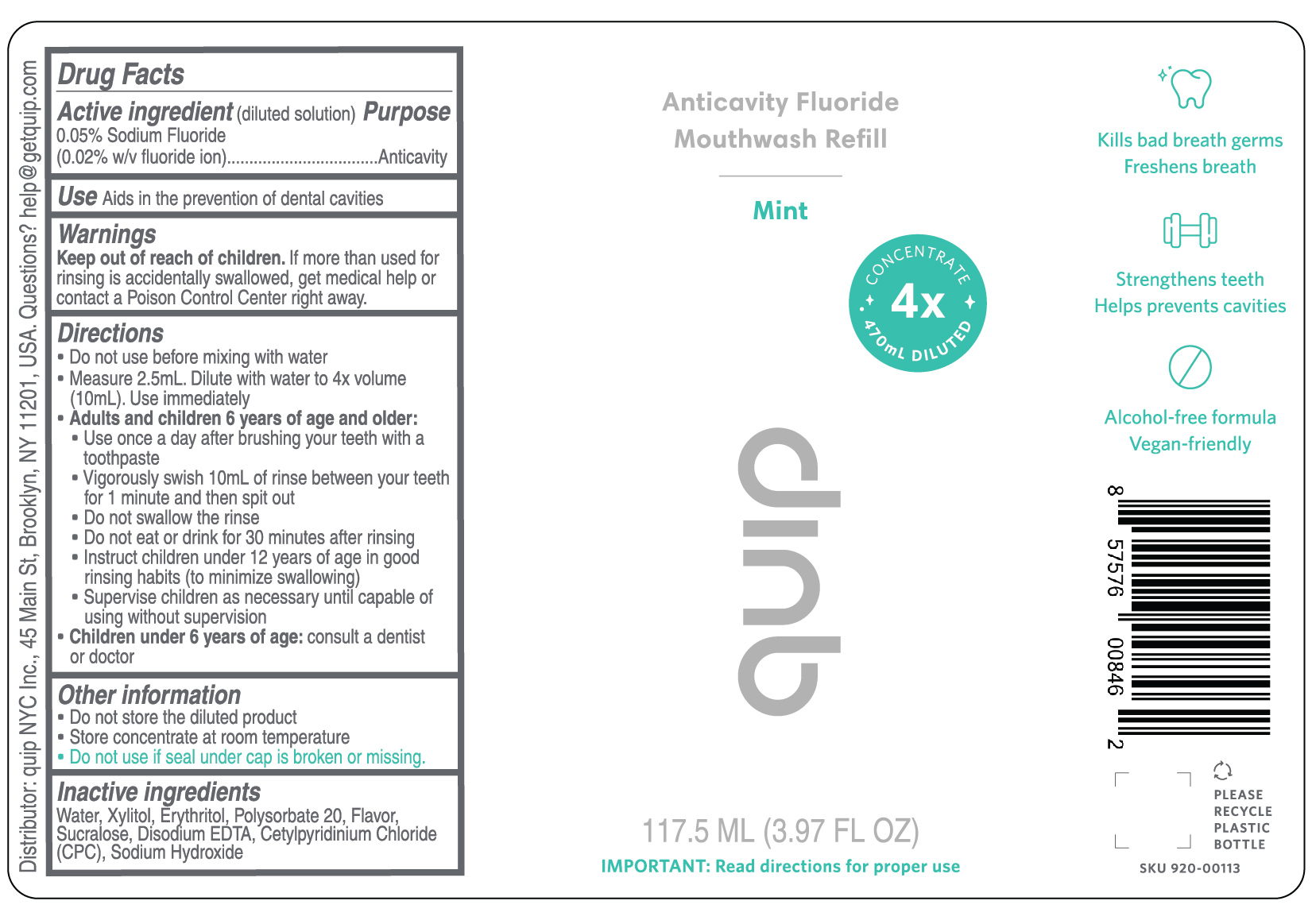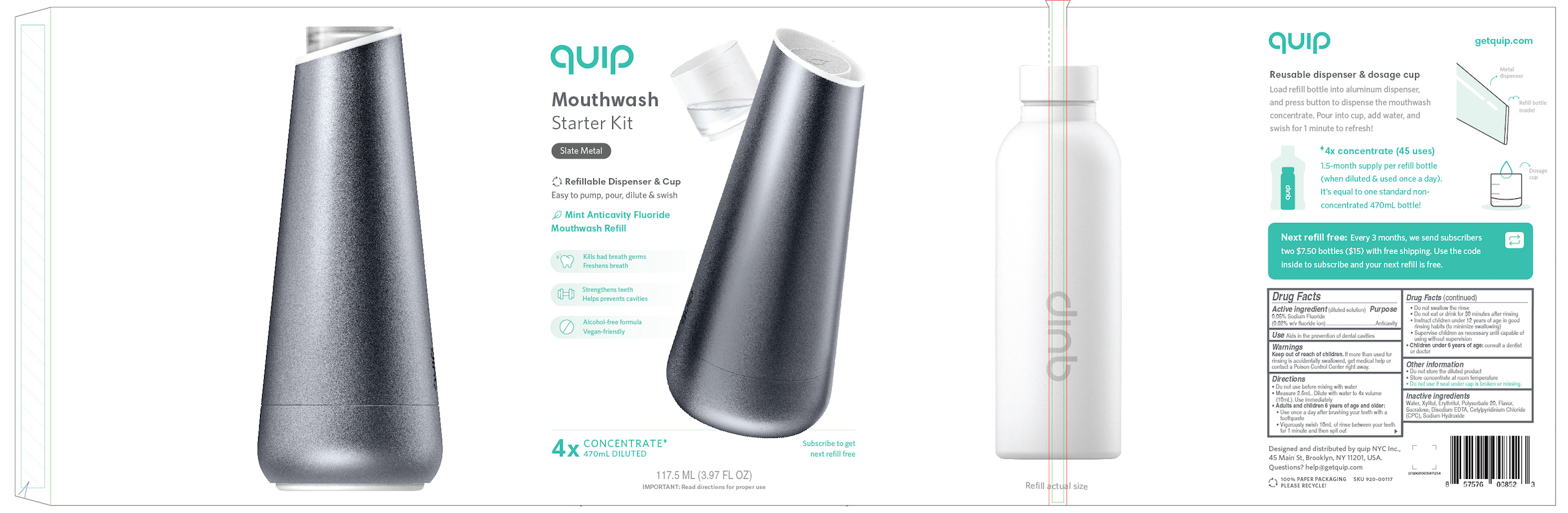 DRUG LABEL: Quip Anticavity Fluoride
NDC: 69261-005 | Form: MOUTHWASH
Manufacturer: Quip NYC Inc.
Category: otc | Type: HUMAN OTC DRUG LABEL
Date: 20250130

ACTIVE INGREDIENTS: SODIUM FLUORIDE 0.05 g/100 mL
INACTIVE INGREDIENTS: EDETATE DISODIUM ANHYDROUS; ERYTHRITOL; WATER; POLYSORBATE 20; XYLITOL; SODIUM HYDROXIDE; SUCRALOSE; CETYLPYRIDINIUM CHLORIDE

Quip Anticavity Fluoride Mouthwash Concentrate

Drug Facts

Active ingredient(diluted solution)

0.05% Sodium fluoride (0.02% w/v fluoride ion)

Purpose

Anticavity

Use

Aids in prevention of dental cavities

Warnings

Keep out of reach of children.If more than used for rinsing is accidentally swallowed, get medical help or contact a Poison Control Center right away.

Directions

- Do not use before mixing with water
- Measure 2.5ml. Dilute with water to 4x volume (10ml). Use immediately
- Adults and children 6 years of age and older:
- Use once a day after brushing your teeth with a toothpaste
- Vigorously swish 10ml of rinse between your teeth for 1 minute and then spit out
- Do not swallow the rinse
- Do not eat or drink for 30 minutes after rinsing
- Supervise children as necessary until capable of using without supervision
- Children under 6 years of age:consult a dentist or doctor

Other information

- Do not store the diluted product
- Store concentrate at room temperature
- Do not use if seal under cap is broken or missing.

Inactive ingredients

Water, Xylitol, Erythritol, Polysorbate 20, Flavor, Sucralose, Disodium EDTA, Cetylpyridinium Chloride, Sodium Hydroxide

Distributed by: quip NYC Inc., 45 Main Street, Brooklyn, NY 11201, USA

Questions?hello@getquip.com

BOTTLE

Anticavity Fluoride Mouthwash Refill
Mint
CONCENTRATE 4x470mL DILUTED
QUIP
117.5 ML (3.97 FL OZ)

IMPORTANT:Read directions for proper use

RETAIL CARTON

QUIP

CONCENTRATE 4x470mL DILUTED

- Kills bad breath germs
- Freshens breath
- Strengthens teeth
- Helps prevent cavities
- Alcohol-free formula
- Vegan-friendly

Anticavity Fluoride Mouthwash Refill
Mint
117.5 ML (3.97 FL OZ)
IMPORTANT: Read directions for proper use

STARTER KIT

QUIP

MouthwashStarter Kit

Refillable Dispenser & Cup

One pump for perfect daily dose

Mint Anticavity Fluoride Mouthwash Refill

Kills bad breath germs
Freshens breath
Strengthens teeth
Helps prevent cavities
Alcohol-free formula
Vegan-friendly

4XCONCENTRATE 470mL DILUTED

117.5 ML (3.97 FL OZ)
IMPORTANT: Read directions for proper use